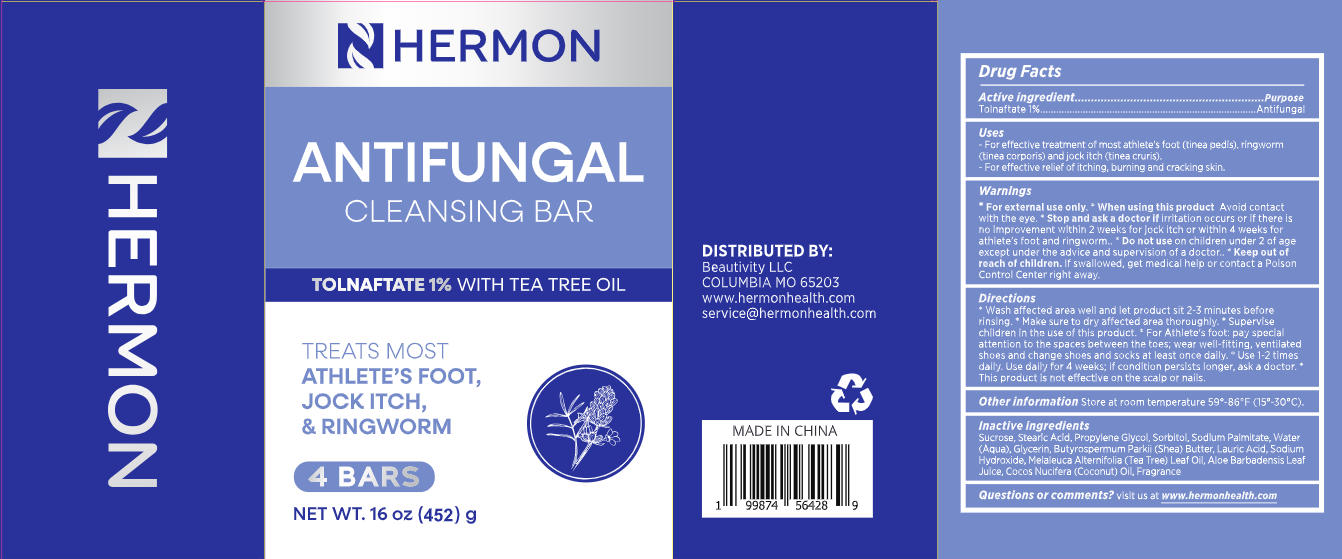 DRUG LABEL: Hermon Antifungal Cleansing Bar
NDC: 85398-029 | Form: SOAP
Manufacturer: Beautivity LLC
Category: otc | Type: HUMAN OTC DRUG LABEL
Date: 20260118

ACTIVE INGREDIENTS: TOLNAFTATE 4.52 g/452 g
INACTIVE INGREDIENTS: GLYCERIN; COCOS NUCIFERA (COCONUT) OIL; SODIUM PALMITATE; SUCROSE; BUTYROSPERMUM PARKII (SHEA) BUTTER; AQUA; SODIUM HYDROXIDE; ALOE BARBADENSIS LEAF JUICE; PROPYLENE GLYCOL; LAURIC ACID; MELALEUCA ALTERNIFOLIA (TEA TREE) LEAF OIL; STEARIC ACID; SORBITOL

85398-029 Initial-149

ACTIVE INGREDIENT

Tolnaftate 1%

PURPOSE

Antifungal

DOSAGE AND ADMINISTRATION

- For effective treatment of most athlete's foot (tinea pedis), ringworm(tinea corporis) and jock itch (tinea cruris).
- For effective relief of itching, burning and cracking skin.

WARNINGS

For external use only

When using this product Avoid contactwith the eye.

Stop and ask a doctor if irritation occurs or if there is no improvement within 2 weeks for jock itch or within 4 weeks for athlete's foot and ringworm.

Do not use on children under 2 of age except under the advice and supervision of a doctor.

KEEP OUT OF REACH OF CHILDREN

If swallowed, get medical help or contact a Poison Control Center right away.

INDICATIONS AND USAGE

- Wash affected area well and let product sit 2-3 minutes beforerinsing.
- Make sure to dry affected area thoroughly.
- Supervisechildren in the use of this product.
- For Athlete's foot: pay special attention to the spaces between the toes; wear well-fitting, ventilated shoes and change shoes and socks at least once daily. *
- Use 1-2 timesdaily. Use daily for 4 weeks; if condition persists longer, ask a doctor.
- This product is not effective on the scalp or nails.

OTHER SAFETY INFORMATION

Store at room temperature 59-86F (15°-30°C).

INACTIVE INGREDIENT

Sucrose, Stearic Acid, Propylene Glycol, Sorbitol, Sodium Palmitate, Water(Aqua),Glycerin, Butyrospermum Parkii (Shea) Butter, Lauric Acid,Sodium Hydroxide, Melaleuca Alternifolia (Tea Tree) Leaf Oil, Aloe Barbadensis LeafJuice, Cocos Nucifera (Coconut) Oil, Fragrance

QUESTIONS

Visit us at www.hermonhealth.com